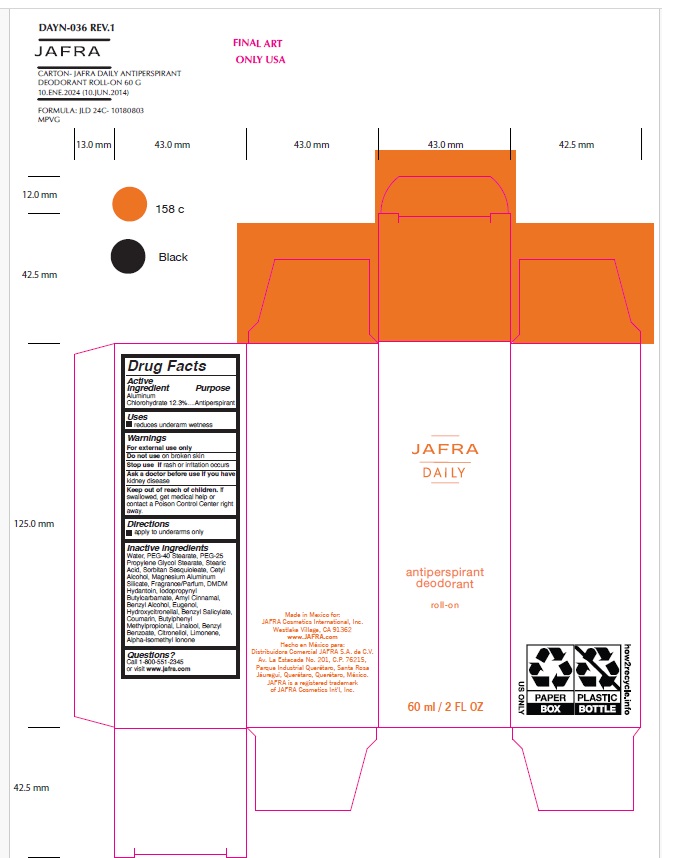 DRUG LABEL: Jafra Daily Antiperspirant Deodorant Roll-on
NDC: 68828-702 | Form: LIQUID
Manufacturer: Distribuidora Comercial Jafra, S.A. de C.V.
Category: otc | Type: HUMAN OTC DRUG LABEL
Date: 20250102

ACTIVE INGREDIENTS: ALUMINUM CHLOROHYDRATE 12.3 g/100 mL
INACTIVE INGREDIENTS: WATER; PEG-40 MONOSTEARATE; PEG-25 PROPYLENE GLYCOL STEARATE; STEARIC ACID; SORBITAN SESQUIOLEATE; MAGNESIUM ALUMINUM SILICATE; DMDM HYDANTOIN; IODOPROPYNYL BUTYLCARBAMATE; CETYL ALCOHOL; .ALPHA.-AMYLCINNAMALDEHYDE; BENZYL ALCOHOL; EUGENOL; HYDROXYCITRONELLAL; BENZYL SALICYLATE; COUMARIN; BUTYLPHENYL METHYLPROPIONAL; LINALOOL, (+/-)-; BENZYL BENZOATE; .BETA.-CITRONELLOL, (R)-; LIMONENE, (+)-; ISOMETHYL-.ALPHA.-IONONE

Jafra Daily Antiperspirant Deodorant Roll-on

Active ingredient

Aluminum Chlorohydrate 12.3%

Purpose

Antiperspirant

Uses

Reduces underarm wetness

Warnings

For external use only
Do not use on broken skin
Stop use if rash or irritation occurs
Ask a doctor before use if you have kidney disease

Keep out of reach of children. If swallowed, get medical help or contact a Poison Control Center right away.

Directions

apply to underarms only

Inactive Ingredients

Water, PEG-40 Stearate, PEG-25 Propylene Glycol Stearate, Stearic Acid, Sorbitan Sesquioleate, Cetyl Alcohol, Magnesium Aluminum Silicate, Fragrance/Parfum, DMDM Hydantoin, Iodopropynyl Butylcarbamate, Amyl Cinnamal, Benzyl Alcohol, Eugenol, Hydroxycitronellal, Benzyl Salicylate, Coumarin, Butylphenyl Methylpropional, Linalool, Benzyl Benzoate, Citronellol, Limonene, Alpha-Isomethyl Ionone

Questions?

Call 1-800-551-2345 or visit www.jafra.com